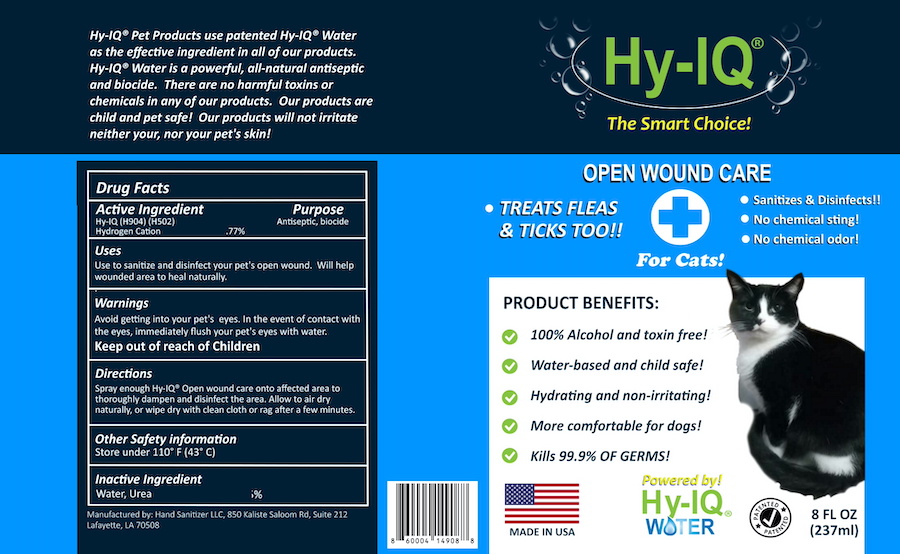 DRUG LABEL: HY IQ OPEN WOUND TREATMENT FOR CATS
NDC: 76701-219 | Form: SPRAY
Manufacturer: HAND SANITIZER LLC
Category: animal | Type: OTC ANIMAL DRUG LABEL
Date: 20210624

ACTIVE INGREDIENTS: HYDROGEN CATION 10 mg/1 mL
INACTIVE INGREDIENTS: WATER 940 mg/1 mL; UREA 50 mg/1 mL

HY IQ OPEN WOUND TREATMENT FOR CATS

ACTIVE INGREDIENT

HY-IQ WATER ([H904] | [H502])
HYDROGEN CATION .77%

PURPOSE

ANTISEPTIC

USES

USE TO SANITIZE AND DISINFECT YOUR PET'S OPEN WOUND. WILL HELP WOUNDED AREA TO HEAL NATURALLY.

WARNINGS

AVOID GETTING INTO YOUR PET'S EYES. IN THE EVENT OF CONTACT WITH THE EYES, IMMEDIATELY FLUSH YOUR PETS'S EYES WITH WATER.
KEEP OUT OF REACH OF CHILDREN

DIRECTIONS

SPRAY ENOUGH HY-IQ® OPEN WOUND CARE ONTO AFFECTED AREA TO THOROUGHLY DAMPEN AND DISINFECT THE AREA. ALLOW TO AIR DRY NATURALLY, OR WIPE DRY WITH CLEAN CLOTH OR RAG AFTER A FEW MINUTES.

OTHER SAFETY INFORMATION

STORE UNDER 110 F (43 C)

INACTIVE INGREDIENTS

WATER, UREA